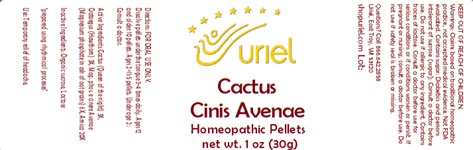 DRUG LABEL: Cactus Cinis Avenae
NDC: 48951-3001 | Form: PELLET
Manufacturer: Uriel Pharmacy Inc.
Category: homeopathic | Type: HUMAN OTC DRUG LABEL
Date: 20240221

ACTIVE INGREDIENTS: SELENICEREUS GRANDIFLORUS STEM 3 [hp_X]/1 1; HAWTHORN LEAF WITH FLOWER 3 [hp_X]/1 1; MAGNESIUM PHOSPHATE, TRIBASIC, PENTAHYDRATE 6 [hp_X]/1 1; ARNICA MONTANA 20 [hp_X]/1 1
INACTIVE INGREDIENTS: SUCROSE; LACTOSE, UNSPECIFIED FORM

Cactus Cinis Avenae

INDICATIONS AND USAGE

Directions: FOR ORAL USE ONLY.

DOSAGE AND ADMINISTRATION

Dissolve pellets under the tongue 3-4 times daily. Ages 12 and older: 10 pellets. Ages 2-11: 5 pellets. Under age 2: Consult a doctor.

ACTIVE INGREDIENT

Active Ingredients: Cactus (Queen of the night) 3X, Crataegus (Hawthorn) 3X, Mag. phos. e cinere Avenae (Magnesium phosphate in ash of oat grains) 6X, Arnica 20X

Inactive Ingredients: Organic sucrose, Lactose

"prepared using rhythmical processes"

PURPOSE

Use: Temporary relief of headache.

KEEP OUT OF REACH OF CHILDREN.

WARNINGS

Warnings: Claims based on traditional homeopathic practice, not accepted medical evidence. Not FDA evaluated. Contains sugar. Diabetics and persons intolerant of sucrose (sugar): Consult a doctor before use. Do not use if allergic to any ingredient. Contains traces of lactose. Consult a doctor before use for serious conditions or if conditions worsen or persist. If pregnant or nursing, consult a doctor before use. Do not use if safety seal is broken or missing.

QUESTIONS

Questions? Call 866.642.2858 Uriel, East Troy, WI 53120 shopuriel.com Lot: